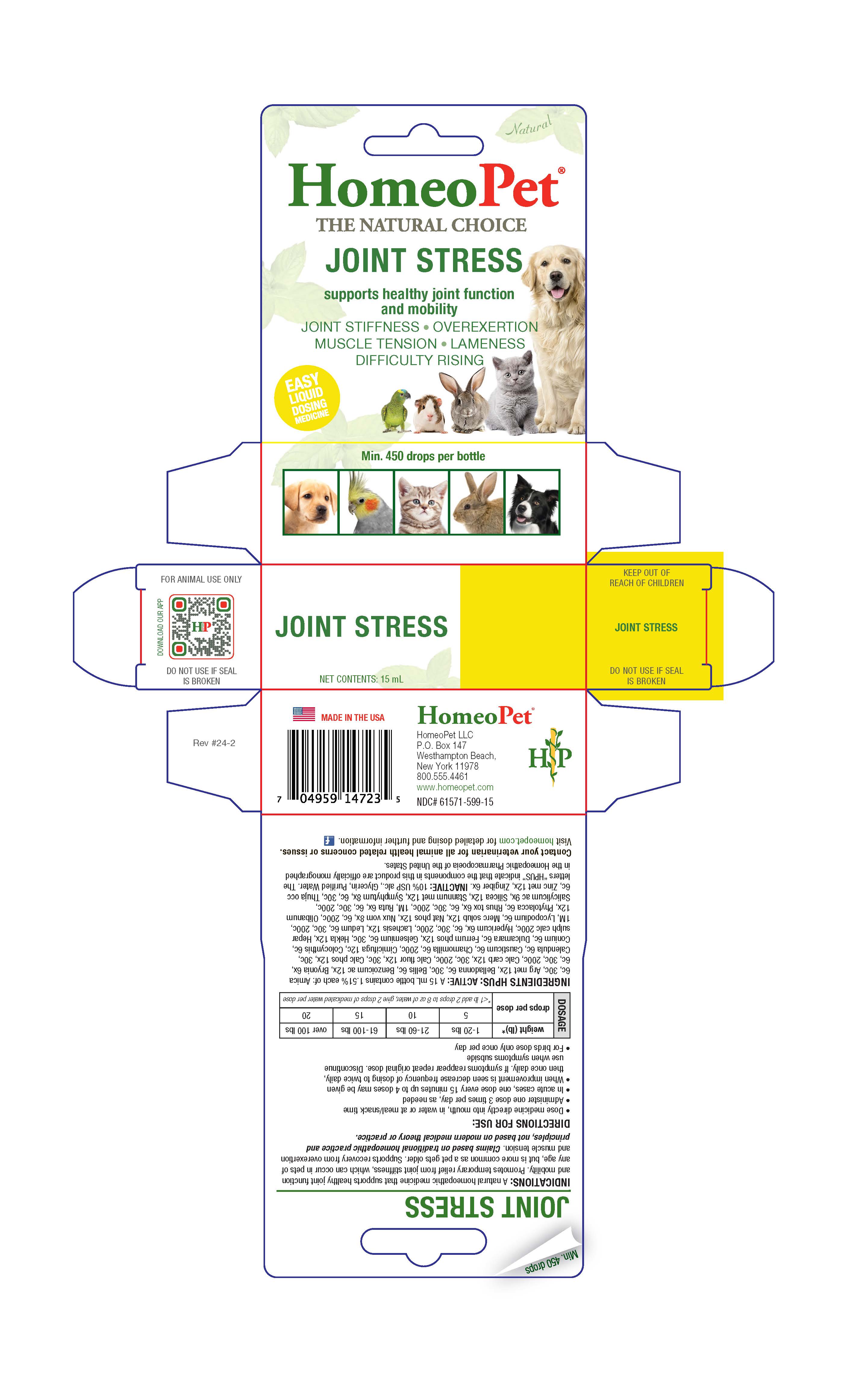 DRUG LABEL: Joint Stress
NDC: 61571-599 | Form: LIQUID
Manufacturer: HomeoPet, LLC
Category: homeopathic | Type: OTC ANIMAL DRUG LABEL
Date: 20241122

ACTIVE INGREDIENTS: ARNICA MONTANA WHOLE 6 [hp_C]/15 mL; SILVER NITRATE 12 [hp_X]/15 mL; ATROPA BELLADONNA WHOLE 6 [hp_C]/15 mL; BELLIS PERENNIS WHOLE 6 [hp_C]/15 mL; BENZOIC ACID 12 [hp_X]/15 mL; BRYONIA ALBA ROOT 6 [hp_X]/15 mL; OYSTER SHELL CALCIUM CARBONATE, CRUDE 12 [hp_X]/15 mL; CALCIUM FLUORIDE 12 [hp_X]/15 mL; TRIBASIC CALCIUM PHOSPHATE 12 [hp_X]/15 mL; CALENDULA OFFICINALIS FLOWERING TOP 6 [hp_C]/15 mL; CAUSTICUM 6 [hp_C]/15 mL; MATRICARIA CHAMOMILLA WHOLE 6 [hp_C]/15 mL; BLACK COHOSH 12 [hp_C]/15 mL; CITRULLUS COLOCYNTHIS FRUIT PULP 6 [hp_C]/15 mL; CONIUM MACULATUM FLOWERING TOP 6 [hp_C]/15 mL; SOLANUM DULCAMARA TOP 6 [hp_C]/15 mL; FERROSOFERRIC PHOSPHATE 12 [hp_X]/15 mL; GELSEMIUM SEMPERVIRENS ROOT 6 [hp_C]/15 mL; HEKLA LAVA 12 [hp_X]/15 mL; CALCIUM SULFIDE 200 [hp_C]/15 mL; HYPERICUM PERFORATUM WHOLE 6 [hp_X]/15 mL; LACHESIS MUTA VENOM 12 [hp_X]/15 mL; RHODODENDRON TOMENTOSUM LEAFY TWIG 6 [hp_C]/15 mL; LYCOPODIUM CLAVATUM SPORE 6 [hp_C]/15 mL; MERCURIUS SOLUBILIS 12 [hp_X]/15 mL; SODIUM PHOSPHATE, DIBASIC, HEPTAHYDRATE 12 [hp_X]/15 mL; STRYCHNOS NUX-VOMICA SEED 8 [hp_X]/15 mL; FRANKINCENSE 12 [hp_X]/15 mL; PHYTOLACCA AMERICANA ROOT 6 [hp_C]/15 mL; TOXICODENDRON PUBESCENS LEAF 6 [hp_X]/15 mL; RUTA GRAVEOLENS FLOWERING TOP 6 [hp_X]/15 mL; SALICYLIC ACID 9 [hp_X]/15 mL; SILICON DIOXIDE 12 [hp_X]/15 mL; TIN 12 [hp_X]/15 mL; COMFREY ROOT 8 [hp_X]/15 mL; THUJA OCCIDENTALIS LEAFY TWIG 6 [hp_C]/15 mL; ZINC 12 [hp_X]/15 mL; GINGER 6 [hp_X]/15 mL
INACTIVE INGREDIENTS: ALCOHOL; GLYCERIN; WATER

Joint Stress

Joint Stress

Supports healthy joint function and mobility

JOINT STIFFNESS-OVEREXERTION

MUSCLE TENSION-LAMENESS

DIFFICULTY RISING

Directions for Use and Dosage

- Dose medicine directly into mouth, in water or at meal/snack time
- Administer one dose 3 times per day, as needed
- In acute cases, one dose every 15 minutes up to 4 doses may be given
- When improvement is seen decrease frequency of dosing to twice daily, then once daily. If symptoms reappear repeat original dose. Discontinue use when symptoms subside
- For birds dose only once per day

Dosage | weight (lb)* | 1-20 lbs | 21-60 lbs | 61-100 lbs | over 100 lbs
Dosage | drops per dose | 5 | 10 | 15 | 20
Dosage | drops per dose | *<1 lb add 2 drops to 8oz of water, give 2 drops of medicated water per dose

Contact Veterinarian

Contact your veterinarian for all animal health related concerns or issues.

Visit homeopet.com for detailed dosing and further information.

Ingredients HPUS: Active

Arnica 6c, 30c, Arg met 12x, Belladonna 6c, 30c, Bellis 6c, Benzoicum ac 12x, Bryonia 6x, 6c, 30c, 200c, Calc carb 12x, 30c, 200c, Calc fluor 12x, 30c, Calc phos 12x, 30c, Calendula 6c, Causticum 6c, Chamomilla 6c, 200c, Cimicifuga 12c, Colocynthis 6c, Conium 6c, Dulcamara 6c, Ferrum phos 12x, Gelsemium 6c, 30c, Hekla 12x, Hepar sulph calc 200c, Hypericum 6x, 6c, 30c, 200c, Lachesis 12x, Ledum 6c, 30c, 200c, 1M, Lycopodium 6c, Merc solub 12x, Nat phos 12x, Nux vom 8x, 6c, 200c, Olibanum 12x, Phytolacca 6c, Rhus tox 6x, 6c, 30c, 200c, 1M, Ruta 6x, 6c, 30c, 200c, Salicylicum ac 9x, Silicea 12x, Stannum met 12x, Symphytum 8x, 6c, 30c, Thuja occ 6c, Zinc met 12x, Zingiber 6x.

Inactive Ingredients

USP Alcohol, Glycerin, Purified Water

Indications

A natural homeopathic medicine that supports healthy joint function and mobility. Promotes temporary relief from joint stiffness, which can occur in pets of any age, but is more common as a pet gets older. Supports recovery from overexertion and muscle tension. Claims based on traditional homeopathic practice and principles, not based on modern medical theory or practice.

PACKAGE LABEL

Add image transcription here...